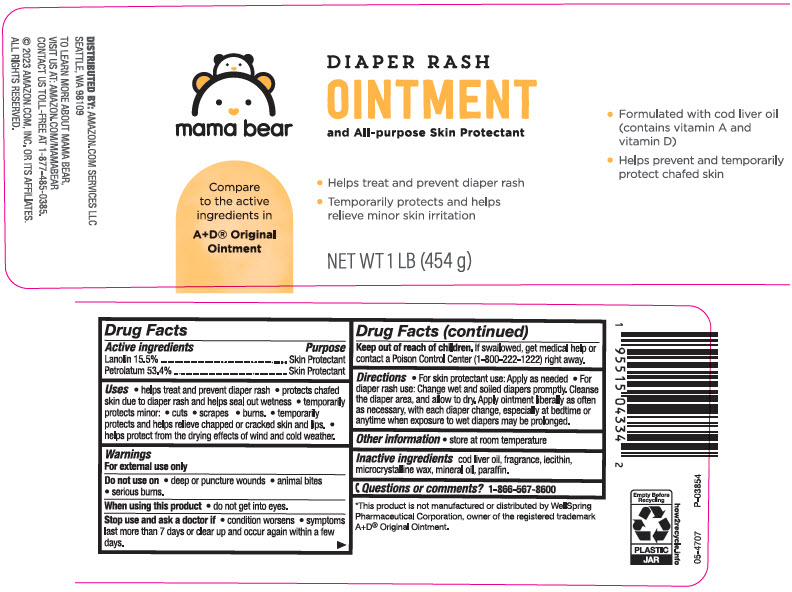 DRUG LABEL: mama bear DIAPER RASH
NDC: 72288-342 | Form: OINTMENT
Manufacturer: AMAZON.COM SERVICES LLC
Category: otc | Type: HUMAN OTC DRUG LABEL
Date: 20240306

ACTIVE INGREDIENTS: Lanolin 155 mg/1 g; Petrolatum 534 mg/1 g
INACTIVE INGREDIENTS: Cod Liver Oil; LECITHIN, SOYBEAN; Microcrystalline Wax; Mineral Oil; Paraffin

mama bear DIAPER RASH OINTMENT
Skin Protectant

Drug Facts

ACTIVE INGREDIENT

Active ingredient | Purpose
Lanolin 15.5% | Skin Protectant
Petrolatum 53.4% | Skin Protectant

Uses

- helps treat and prevent diaper rash
- protects chafed skin due to diaper rash and helps seal out wetness
- temporarily protects minor.
- cuts
- scrapes
- burns.
- temporarily protects and helps relieve chapped or cracked skin and lips.
- helps protect from the drying effects of wind and cold weather.

Warnings

For external use only

Do not use on

- deep or puncture wounds
- animal bites
- serious burns.

When using this product

- do not get into eyes.

Stop use and ask a doctor if

- condition worsens
- symptoms last more than 7 days or clear up and occur again within a few days.

Keep out of reach of children. If swallowed, get medical help or contact a Poison Control Center (1-800-222-1222) immediately.

Directions

- For skin protectant use: Apply as needed
- For diaper rash use: Change wet and soiled diapers promptly. Cleanse the diaper area, and allow to dry. Apply ointment liberally as often a as necessary, with each diaper change, especially at bedtime or anytime when exposure to wet diapers may be prolonged.

Other information

store at room temperature

Inactive ingredients

cod liver oil, fragrance, lecithin, microcrystalline wax, mineral oil, paraffin.

Questions or comments? 1-866-567-8600

DISTRIBUTED BY: AMAZON.COM SERVICES LLC
SEATTLE, WA 98109

PRINCIPAL DISPLAY PANEL - 454 g Jar Label

mama bear

Compare
to the active
ingredients in
A+D® Original
Ointment

DIAPER RASH
OINTMENT
and All-purpose Skin Protectant

- Helps treat and prevent diaper rash
- Temporarily protects and helps
  relieve minor skin irritation

NET WT 1 LB (454 g)

- Formulated with cod liver oil
  (contains vitamin A and
  vitamin D)
- Helps prevent and temporarily
  protect chafed skin